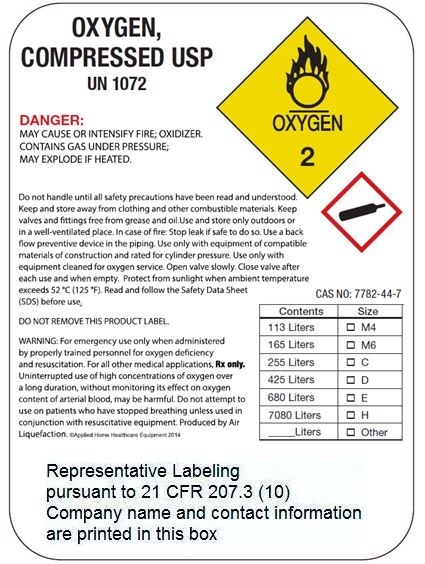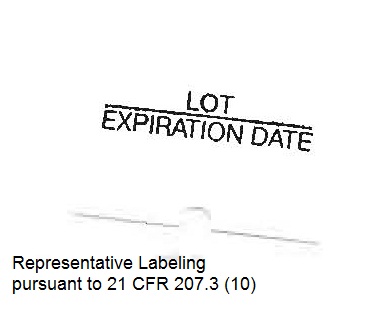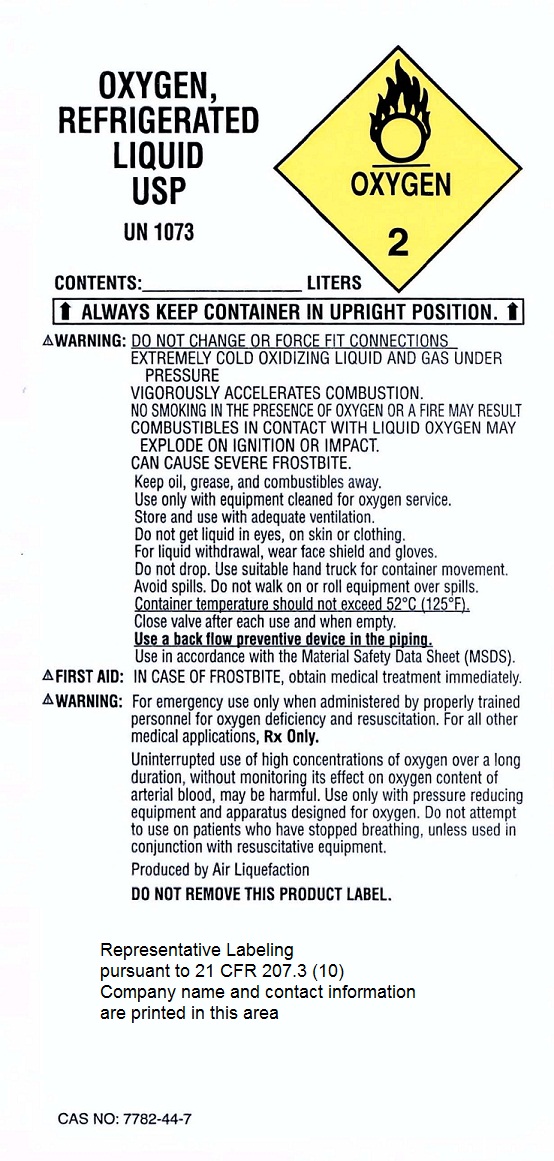 DRUG LABEL: Oxygen
NDC: 72712-001 | Form: GAS
Manufacturer: Liquid O2 Transfills, Inc.
Category: prescription | Type: HUMAN PRESCRIPTION DRUG LABEL
Date: 20250210

ACTIVE INGREDIENTS: OXYGEN 99 L/100 L

Oxygen

Principal for Oxygen Product

OXYGEN,

REFRIGERATED

LIQUID USP

UN 1073

CONTENTS ________________LITERS

CAS NO: 7782-44-7

DANGER:

REFRIGERATED LIQUEFIED OXIDIZING GAS. ALWAYS

KEEP CONTAINER IN UPRIGHT POSITION. DO NOT

CHANGE OR FORCE FIT CONNECTIONS. MAY CAUSE OR INTENSIFY

FIRE; OXIDIZER, CONTAINS REFRIGERATED GAS: MAY CAUSE

CRYOGENIC BURNS OR INJURY. COMBUSTIBLES IN CONTACT WITH

LIQUID OXYGEN MAY EXPLODE ON IGNITION OR IMPACT.

Do not get in eyes, on skin, or on clothing. Keep reduction valves free

from grease and oil. In case of fire, stop leak if safe to do so. Avoid

spills. Do not walk or roll equipment over spills. Store and use in a well

ventilated place. Use only with equipment of compatible materials

of construction and rated for cylinder pressure. Wear cold insulating

gloves/face shield/eye protection. Protect from sunlight when ambient

temperature exceeds 52 F. Container temperature should

not exceed 52 F. Close valve after each use and when

empty. Use a back flow preventative device in the piping. Do not

handle until all safety precautions have been read and understood.

Use only with equipment cleaned for oxygen service. Keep/store away

from combustible materials. Do not drop. Use suitable hand truck for

container movement.

FIRST AID:

IN CASE OF FROSTBITE: Thaw frosted parts with lukewarm water.

Do not rub affected area. Get immediate medical advice/attention.

DO NOT REMOVE THIS PRODUCT LABEL.

For emergency use only when administered by properly trained

personnel for oxygen deficiency and resuscitation. For all other medical

applications, Rx only. Uninterrupted use of high concentrations of

oxygen over a long duration, without monitoring its effect on oxygen

content of arterial blood, may be harmful. Use only with pressure

reducing equipment and apparatus designed for oxygen. Do not

attempt to use on patients who have stopped breathing unless used in

conjunction with resuscitative equipment. Produced by Air Liquefaction.

ALWAYS KEEP CONTAINER IN UPRIGHT POSITION

OXYGEN

COMPRESSED

USP

UN 1072

DANGER:

MAY CAUSE OR INTENSIFY FIRE; OXIDIZER. CONTAINS GAS UNDER PRESSURE; MAY EXPLODE IF HEATED.
Do not handle until all safety precautions have been read and understood. Keep and store away from clothing and other combustible materials. Keep valves and fittings free from grease and oil. Use and store only outdoors or in a well-ventilated place. In case of fire: Stop leak if safe to do so. Use a back flow preventive device in the piping. Use only with equipment of compatible materials of construction and rated for cylinder pressure. Use only with equipment cleaned for oxygen service. Open valve slowly. Close valve after each use and when empty. Protect from sunlight when ambient temperature exceeds 52 °c (125 °F). Read and follow the Safety Data Sheet (SDS) before use.

CAS NO: 7782-44-7

DO NOT REMOVE THIS PRODUCT LABEL.

WARNING: For emergency use only when administered by properly trained personnel for oxygen deficiency

and resuscitation. For all other medical applications, Rx only.

Uninterrupted use of high concentrations of oxygen over a long duration, without monitoring its effect on oxygen

content of arterial blood, may be harmful. Do not attempt to use on patients who have stopped breathing unless used in conjunction with resuscitative equipment. Produced by Air Liquefaction.